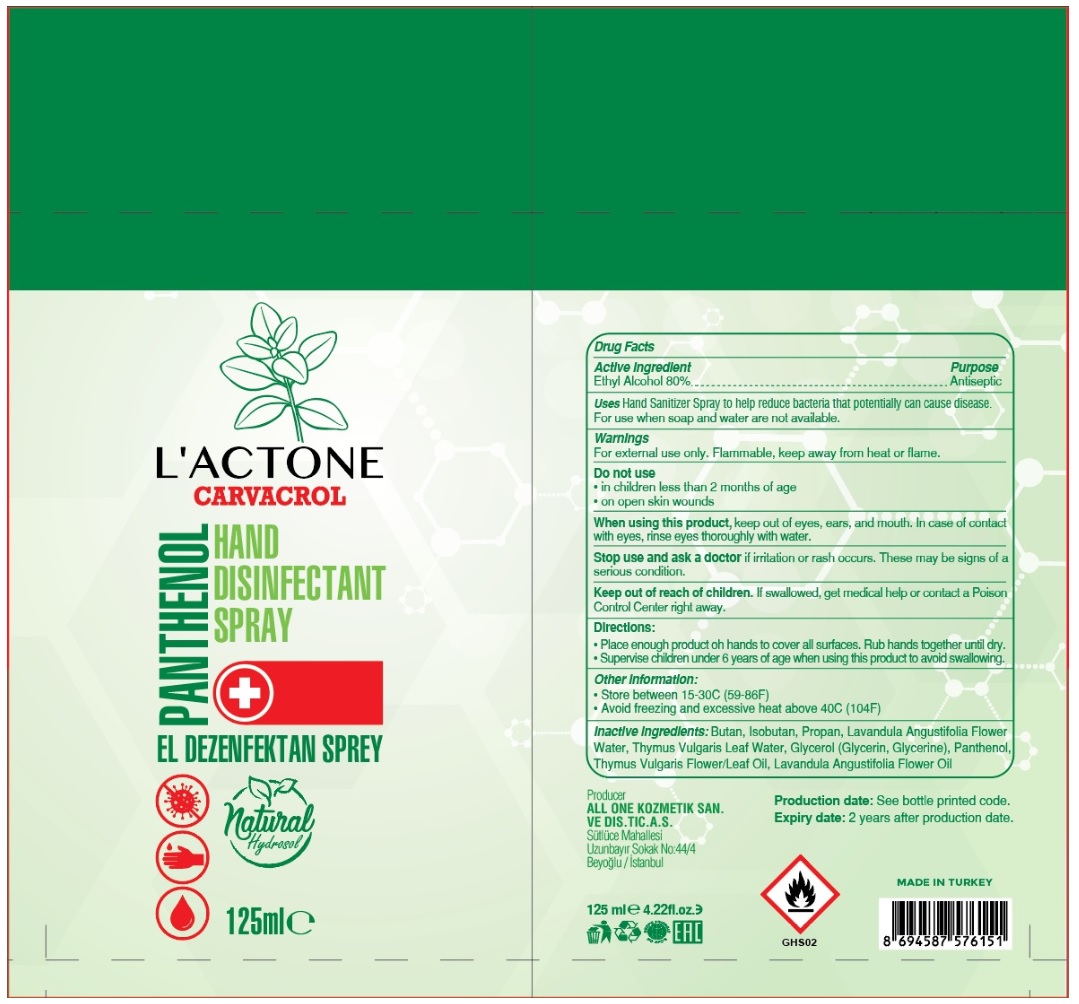 DRUG LABEL: LACTONE CARVACROL HAND DISINFECTANT
NDC: 75348-560 | Form: SPRAY
Manufacturer: ALL ONE KOZMETIK SANAYI DIS TICARET ANONIM SIRKETI
Category: otc | Type: HUMAN OTC DRUG LABEL
Date: 20200528

ACTIVE INGREDIENTS: ALCOHOL 80 mL/100 mL
INACTIVE INGREDIENTS: BUTANE; ISOBUTANE; PROPANE; LAVANDULA ANGUSTIFOLIA SUBSP. ANGUSTIFOLIA WHOLE; THYME OIL; GLYCERIN; PANTHENOL

L'ACTONE CARVACROL HAND DISINFECTANT SPRAY

Active ingredient

Ethyl Alcohol 80%

Purpose

Antiseptic

Uses

Hand Sanitizer Spray to help reduce bacteria that potentially can cause disease. For use when soap and water are not available.

Warnings

For external use only. Flammable, keep away from heat or flame.

Do not use

- in children less than 2 months of age
- on open skin wounds

When using this product, keep out of eyes, ears, and mouth. In case of contact with eyes, rinse eyes thoroughly with water.

Stop use and ask a doctor if irritation or rash occurs. These may be signs of a serious condition.

Keep out of reach of children.

If swallowed, get medical help or contact a Poison Control Center right away.

Directions:

- Place enough product on hands to cover all surfaces. Rub hands together until dry.
- Supervise children under 6 years of age when using this product to avoid swallowing.

Other Information:

- Store between 15-30C (59-86F)
- Avoid freezing and excessive heat above 40C (104F)

Inactive ingredients:

Butan, Isobutan, Propan, Lavandula Angustifolia Flower Water, Thymus Vulgaris Leaf Water, Glycerol (Glycerin, Glycerine), Panthenol, Thymus Vulgaris Flower/Leaf Oil, Lavandula Angustifolia Flower Oil

Producer

ALL ONE KOZMETIL SAN. VE DIS. TIC.A.S

Sutluce Mahallesi

Uzunbayir Sokak No:44/4

Beyoglu/Istanbul

Production date: See bottle printed code.

Expiry date: 2 years after production date.

MADE IN TURKEY

PANTHENOL

EL DEZENFEKTAN SPREY

natural hydrosol